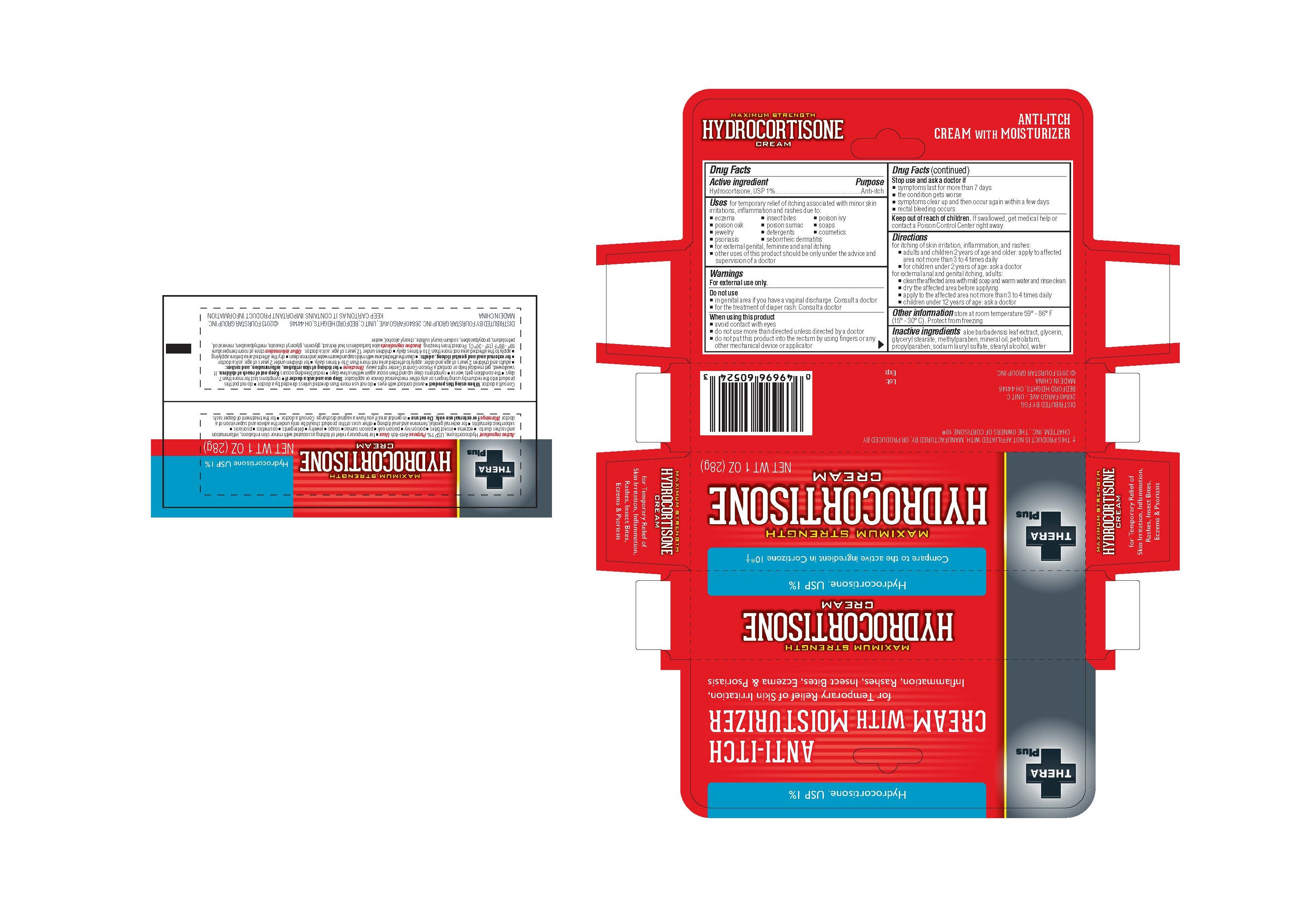 DRUG LABEL: 
                  Thera
                
                  

NDC: 55621-001 | Form: CREAM
Manufacturer: Zhejiang Jingwei Pharmaceutical Co., Ltd.
Category: otc | Type: HUMAN OTC DRUG LABEL
Date: 20231025

ACTIVE INGREDIENTS: HYDROCORTISONE 1 g/100 g
INACTIVE INGREDIENTS: ALOE VERA LEAF; GLYCERIN; GLYCERYL MONOSTEARATE; METHYLPARABEN; MINERAL OIL; PETROLATUM; PROPYLPARABEN; SODIUM LAURYL SULFATE; STEARYL ALCOHOL; WATER

Drug Facts

INACTIVE INGREDIENT

aloe barbadensis leaf extract, glycerin, glyceral stearate, methylparaben, mineral oil, petrolatum, propylparaben, sodium lauryl sulfate, stearyl alcohol, water Inactive Ingredients

Active Ingredient

Hydrocortisone, USP 1%

Purpose

Anti-itch

INDICATIONS AND USAGE

- for temporary relief of itching associated with minor skin irritations,inflammation and rashes due to: Uses

- eczema -insect bites -poison ivy

-poison oak -poison sumac -soaps

-jewelry -detergents -cosmetics

-psoriasis -seborrheic dermatisis

-for external genital, feminine and anal itching

-other uses of this product should be only under the advice and supervision of a doctor

KEEP OUT OF REACH OF CHILDREN

. If swallowed, get medical help or contact a Poison Control Center right away. Keep out of reach of children

Warnings for external use only

Do not use

-in genital area if you have a vaginal discharge. Consult a doctor

-for the treatment of diaper rash. Consult a doctor

Stop use and ask a doctor if

-symptoms last for more than 7 days

-the condition gets worse

-symptoms clear up and then occur again within a few days

-rectal bleeding occurs

When using this product

-avoid contact with eyes

-do not use more than directed unless directed by a doctor

-do not put this product into the rectum by using fingers or any other mechanical device or applicator

Directions

for itching of skin irritation, inflammation and rashes:

-adults and children 2 years of age and older: apply to the affected areanot more than 3 to 4 times dailt

-for children udner 2 years of age: ask a doctor

for external anal and genital itching, adults:

-clean the affected area with mild soap and warm water and rinse clean.

-dry the affected area before applying

-apply to the affected area not mroe than 3 to 4 times daily

-children under 12 years of age: ask a doctor